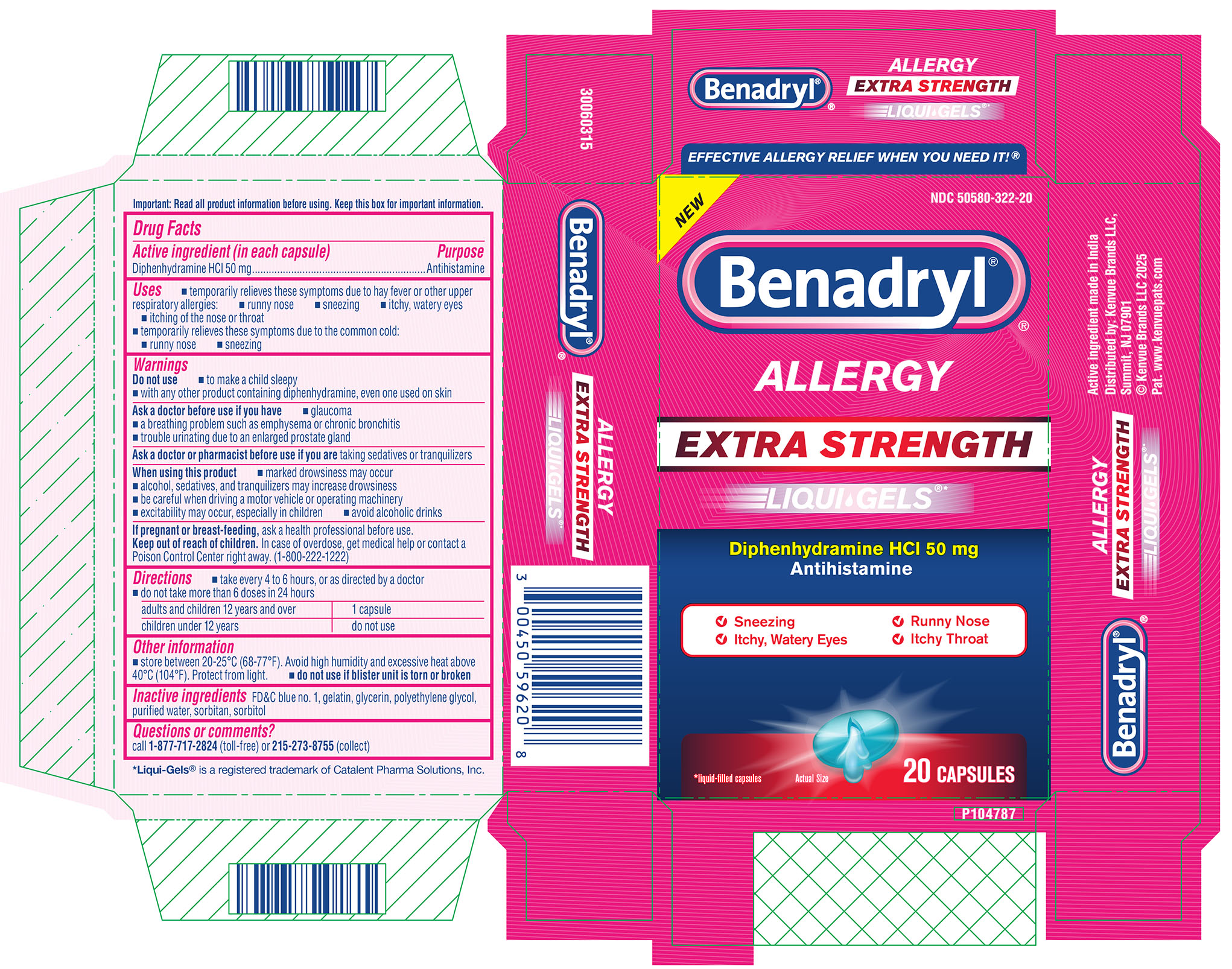 DRUG LABEL: Benadryl Allergy Extra Strength Liqui-Gels
NDC: 50580-322 | Form: CAPSULE, LIQUID FILLED
Manufacturer: Kenvue Brands LLC
Category: otc | Type: HUMAN OTC DRUG LABEL
Date: 20251203

ACTIVE INGREDIENTS: DIPHENHYDRAMINE HCL 50 mg/1 1
INACTIVE INGREDIENTS: GLYCERIN; SORBITAN; SORBITOL; FD&C BLUE NO. 1; WATER; GELATIN; POLYETHYLENE GLYCOL, UNSPECIFIED

Benadryl Allergy Extra Strength Liqui-Gels

Drug Facts

Active ingredient (in each capsule)

Diphenhydramine HCl 50 mg

Purpose

Antihistamine

Uses

- temporarily relieves these symptoms due to hay fever or other upper respiratory allergies:

runny nose

sneezing

itchy, watery eyes

itching of the nose or throat

- temporarily relieves these symptoms due to the common cold:

runny nose

sneezing

Warnings

Do not use

- to make a child sleepy
- with any other product containing diphenhydramine, even one used on skin

Ask a doctor before use if you have

- glaucoma
- a breathing problem such as emphysema or chronic bronchitis
- trouble urinating due to an enlarged prostate gland

Ask a doctor or pharmacist before use if you are

taking sedatives or tranquilizers

When using this product

- marked drowsiness may occur
- alcohol, sedatives, and tranquilizers may increase drowsiness
- be careful when driving a motor vehicle or operating machinery
- excitability may occur, especially in children
- avoid alcoholic drinks

If pregnant or breast-feeding, ask a health professional before use.

Keep out of reach of children

In case of overdose, get medical help or contact a Poison Control Center right away. (1-800-222-1222)

Directions

- take every 4 to 6 hours, or as directed by a doctor
- do not take more than 6 doses in 24 hours

adults and children 12 years and over | 1 capsule
children under 12 years | do not use

Other information

- store between 20-25°C (68-77°F). Avoid high humidity and excessive heat above 40°C (104°F). Protect from light.
- do not use if blister unit is torn or broken

Inactive ingredients

FD&C blue no. 1, gelatin, glycerin, polyethylene glycol, purified water, sorbitan, sorbitol

Questions or comments?

call 1-877-717-2824 (toll-free) or 215-273-8755 (collect)

PRINCIPAL DISPLAY PANEL

NEW

NDC 50580-322-20

Benadryl®

ALLERGY®

EXTRA STRENGHT

LIQUI GELS®*

Diphenhydramine HCl 50 mg

Antihistamine

Sneezing

Runny Nose

Itchy, Watery Eyes

Itchy Throat

*liquid-filled capsules

Actual Size

20 CAPSULES